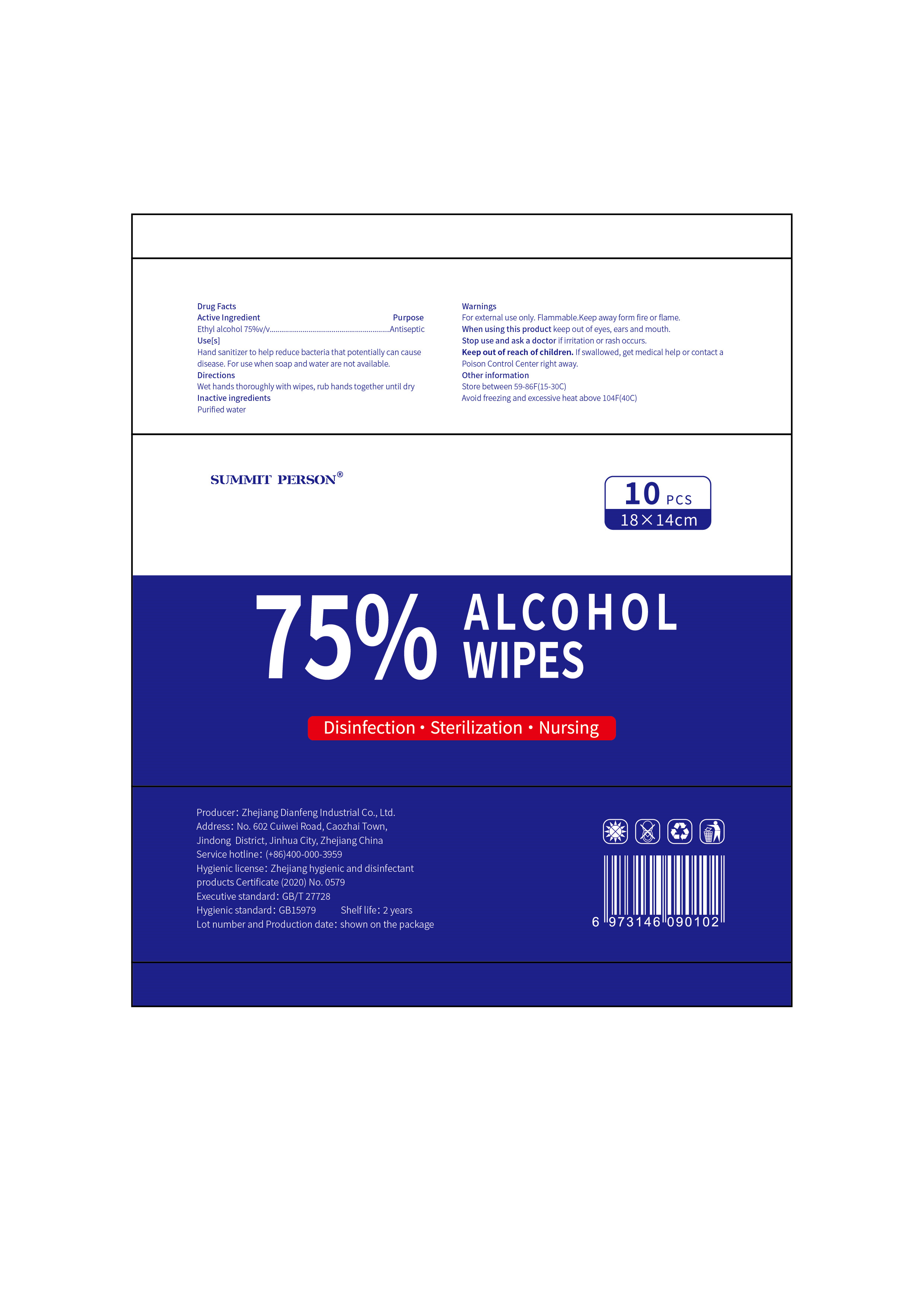 DRUG LABEL: alcohol wipes
NDC: 81648-001 | Form: CLOTH
Manufacturer: Zhejiang Dianfeng Industrial Co., Ltd.
Category: otc | Type: HUMAN OTC DRUG LABEL
Date: 20210304

ACTIVE INGREDIENTS: ALCOHOL 75 mL/100 mL
INACTIVE INGREDIENTS: WATER

ACTIVE INGREDIENT

Ethyl alcohol

PURPOSE

Antiseptic

Use[s]

Hand sanitizer to help reduce bacteria that potentially can cause disease.For use when soap and water are not available.

Stop use and ask a doctor if irritation or rash occurs.

Keep out of reach of children. lf swallowed, get medical help or contact a Poison Control Center right away.

When using this product keep out of eyes,ears and mouth.

Directions

wet hands thoroughly with wipes, rub hands together until dry

INACTIVE INGREDIENT

Purified water

other information

Store between 59-86°F(15-30°C)
Avoid freezing and excessive heat above 104°F(40°C)

WARNINGS

For external use only. Flammable.Keep away form fire or flame.